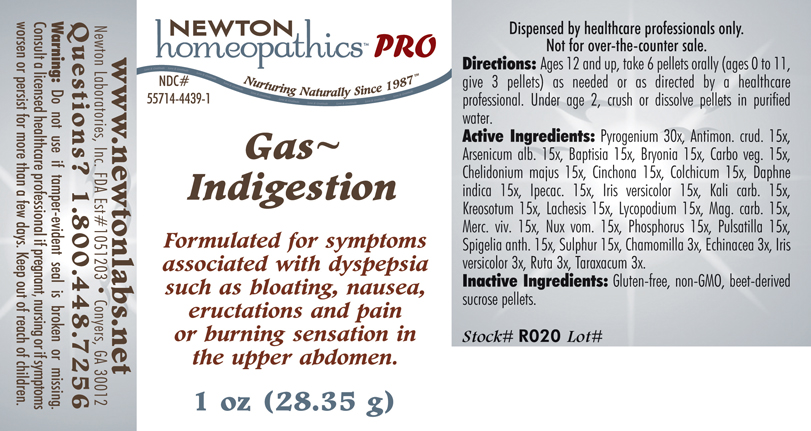 DRUG LABEL: Gas - Indigestion 
NDC: 55714-4439 | Form: PELLET
Manufacturer: Newton Laboratories, Inc.
Category: homeopathic | Type: HUMAN PRESCRIPTION DRUG LABEL
Date: 20110601

ACTIVE INGREDIENTS: Rancid Beef 30 [hp_X]/1 g; Antimony Trisulfide 15 [hp_X]/1 g; Arsenic Trioxide 15 [hp_X]/1 g; Baptisia Tinctoria Root 15 [hp_X]/1 g; Bryonia Alba Root 15 [hp_X]/1 g; Activated Charcoal 15 [hp_X]/1 g; Chelidonium Majus 15 [hp_X]/1 g; Cinchona Officinalis Bark 15 [hp_X]/1 g; Colchicum Autumnale Bulb 15 [hp_X]/1 g; Daphne Odora Bark 15 [hp_X]/1 g; Ipecac 15 [hp_X]/1 g; Iris Versicolor Root 15 [hp_X]/1 g; Potassium Carbonate 15 [hp_X]/1 g; Wood Creosote 15 [hp_X]/1 g; Lachesis Muta Venom 15 [hp_X]/1 g; Lycopodium Clavatum Spore 15 [hp_X]/1 g; Magnesium Carbonate 15 [hp_X]/1 g; Mercury 15 [hp_X]/1 g; Strychnos Nux-vomica Seed 15 [hp_X]/1 g; Phosphorus 15 [hp_X]/1 g; Pulsatilla Vulgaris 15 [hp_X]/1 g; Spigelia Anthelmia 15 [hp_X]/1 g; Sulfur 15 [hp_X]/1 g; Matricaria Recutita 3 [hp_X]/1 g; Echinacea, Unspecified 3 [hp_X]/1 g; Ruta Graveolens Flowering Top 3 [hp_X]/1 g; Taraxacum Officinale 3 [hp_X]/1 g
INACTIVE INGREDIENTS: Sucrose

Gas - Indigestion

INDICATIONS & USAGE SECTION

Gas - Indigestion Formulated for symptoms associated with dyspepsia such as bloating, nausea, eructations and pain or burning sensation in the upper abdomen.

DOSAGE & ADMINISTRATION SECTION

Directions: Ages 12 and up, take 6 pellets orally (ages 0 to 11, give 3 pellets) as needed or as directed by a healthcare professional. Under age 2, crush or dissolve pellets in purified water.

ACTIVE INGREDIENT SECTION

Pyrogenium 30x, Antimon. crud. 15x, Arsenicum alb. 15x, Baptisia 15x, Bryonia 15x, Carbo veg. 15x, Chelidonium majus 15x, Cinchona 15x, Colchicum 15x, Daphne indica 15x, Ipecac. 15x, Iris versicolor 15x, Kali carb. 15x, Kreosotum 15x, Lachesis 15x, Lycopodium 15x, Mag. carb. 15x, Merc. viv. 15x, Nux vom. 15x, Phosphorus 15x, Pulsatilla 15x, Spigelia anth. 15x, Sulphur 15x, Chamomilla 3x, Echinacea 3x, Iris versicolor 3x, Ruta 3x, Taraxacum 3x.

PURPOSE SECTION

Formulated for symptoms associated with dyspepsia such as bloating, nausea, eructations and pain or burning sensation in the upper abdomen.

INACTIVE INGREDIENT SECTION

Inactive Ingredients: Gluten-free, non-GMO, beet-derived sucrose pellets.

QUESTIONS? SECTION

www.newtonlabs.net Newton Laboratories, Inc. FDA Est # 1051203 - Conyers, GA 30012
Questions? 1.800.448.7256

WARNINGS SECTION

Warning: Do not use if tamper - evident seal is broken or missing. Consult a licensed healthcare professional if pregnant, nursing or if symptoms worsen or persist for more than a few days. Keep out of reach of children.

PREGNANCY OR BREAST FEEDING SECTION

Consult a licensed healthcare professional if pregnant, nursing or if symptoms worsen or persist for more than a few days.

KEEP OUT OF REACH OF CHILDREN SECTION

Keep out of reach of children.